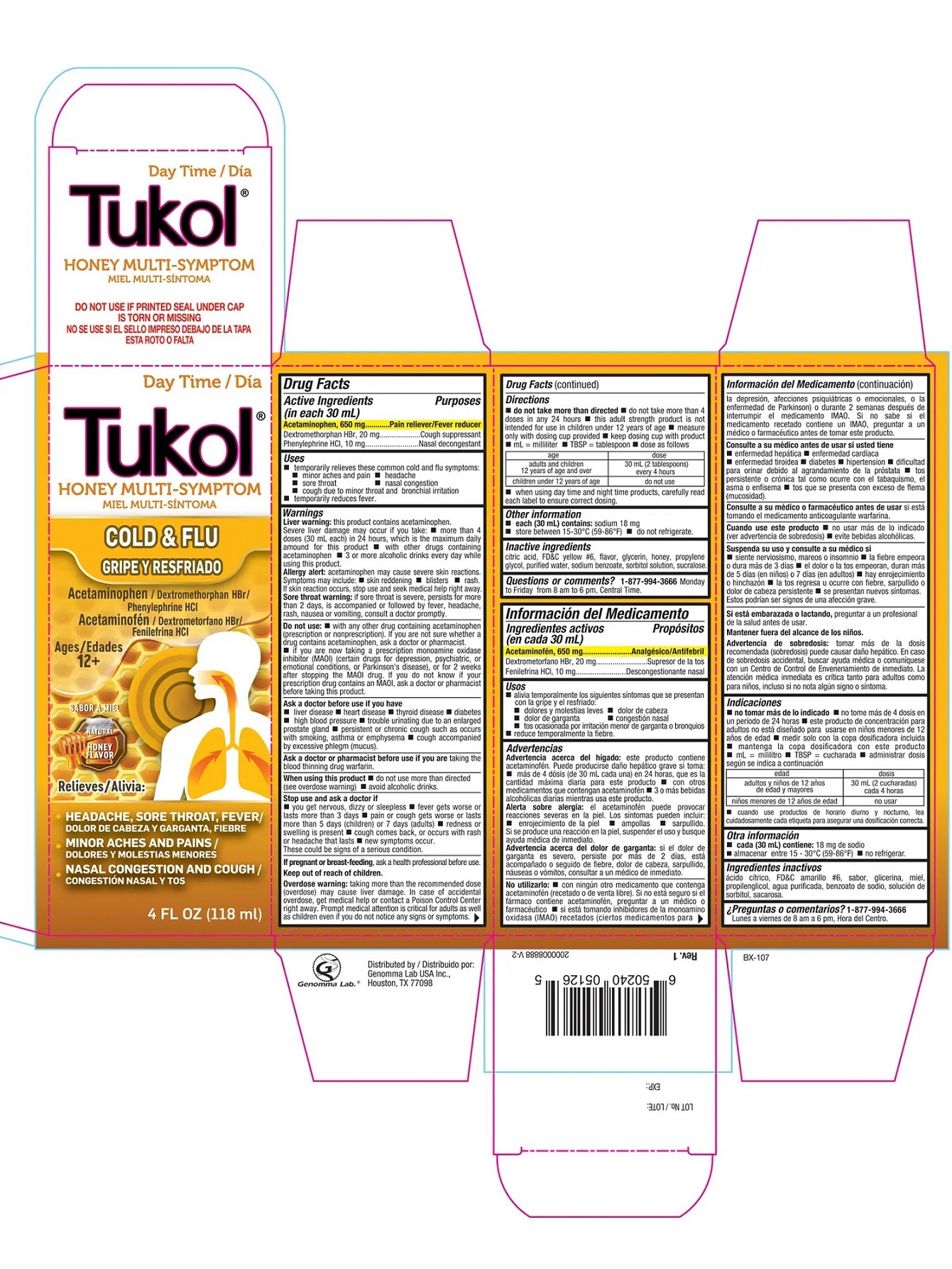 DRUG LABEL: Tukol Honey Daytime Cold and Flu
NDC: 50066-302 | Form: SYRUP
Manufacturer: Genomma Lab USA
Category: otc | Type: HUMAN OTC DRUG LABEL
Date: 20241021

ACTIVE INGREDIENTS: ACETAMINOPHEN 21.667 mg/1 mL; DEXTROMETHORPHAN HYDROBROMIDE 0.667 mg/1 mL; PHENYLEPHRINE HYDROCHLORIDE 0.333 mg/1 mL
INACTIVE INGREDIENTS: WATER; GLYCERIN; PROPYLENE GLYCOL; SORBITOL; SODIUM BENZOATE; SUCRALOSE; ANHYDROUS CITRIC ACID; FD&C YELLOW NO. 6; HONEY

Tukol®Honey Daytime Cold & Flu

Drug Facts

ACTIVE INGREDIENT

Active Ingredients (in each 30 mL) | Purpose
Acetaminophen 650 mg | Pain reliever/Fever reducer
Dextromethorphan HBr 20 mg | Cough suppressant
Phenylephrine HCl 10 mg | Nasal Decongestant

Uses

Temporarily relieves cold/flu symptoms:

- minor aches and pain
- headache
- sore throat
- nasal congestion
- cough due to minor throat and bronchial irritation
- temporarily reduces fever

Warnings

Liver warning

The product contains Acetaminophen. Severe liver damage may occur if you take

- more than 4 doses (30 mL each) in 24 hours, which is the maximum daily amount for this product
- with other drugs containing acetaminophen
- 3 or more alcoholic drinks every day while using this product

Allergy alert

Acetaminophen may cause severe skin reactions. Symptoms may include

- skin reddening
- blisters
- rash.

If skin reaction occurs, stop use and seek medical help right away.

Sore throat warning

If sore throat is severe, persists for more than 2 days, is accompanied or followed by fever, headache, rash, nausea or vomiting, consult a doctor promptly.

Do not use

- with any other drug containing acetaminophen (prescription or nonprescription). If you are not sure whether a drug contains acetaminophen, ask a doctor or pharmacist
- if you are now taking a prescription monoamine oxidase inhibitor (MAOI) (certain drugs for depression, psychiatric, or emotional conditions, or Parkinson's disease), or for two weeks after stopping the MAOI drug. If you do not know if your prescription drug contains an MAOI, ask a doctor or pharmacist before taking this product.

Ask a doctor before use if you have

- liver disease
- heart disease
- thyroid disease
- diabetes
- high blood pressure
- trouble urinating due to an enlarged prostate gland
- persistent or chronic cough such as occurs with smoking, asthma or emphysema
- cough accompanied by excessive phlegm (mucus)

Ask a doctor or pharmacist before use

- if you are taking the blood thinning drug warfarin

When using this product

- do not use more than directed (see overdose warning)
- avoid alcoholic drinks

Stop use and ask a doctor if

- you get nervous, dizzy or sleepless
- fever gets worse or lasts more than 3 days
- pain or cough gets worse or lasts more than 5 days (children) or 7 days (adults)
- redness or swelling is present
- cough comes back, or occurs with rash or headache that lasts.
- new symptoms occur
- These could be signs of a serious condition.

PREGNANCY OR BREAST FEEDING

If pregnant or breast feeding,ask a health professional before use.

Keep out of reach of children.

Overdose warning

Taking more than the recommended dose (overdose) may cause liver damage. In case of accidental overdose, get medical help or contact a Poison Control Center right away. Prompt medical attention is critical for adults as well as children even if you do not notice any signs or symptoms.

Directions

- do not take mare than directed
- do not take more than 4 doses in any 24 hours
- this adult strength product is not inteded for use in children under 12 years of age
- measyre only with dosing cup provided
- keep dosing cup with product
- mL = mililiter
- TBSP = tablespoon
- dose as follows

age | dose
adults and children 12 years of age and over | 30 mL (2 tablespoons) every 4 hours
Children under 12 years | Do not use

- When using Day Time and Night Time products, carefully read each label to ensure correct dosing.

Other information

- each 30 mL contains sodium: 18 mg
- store between 15-30oC (59-86oF)
- do not refrigerate

Inactive ingredients

Citric acid, FD&C Yellow # 6, flavor, glycerin, honey, propylene glycol, purified water, sodium benzoate, sorbitol solution, sucralose

Questions or comments?

1-877-994-3666 Monday to Friday from 8 am to 6 pm, Central Time.

Distributed by
Genomma Lab USA Inc.,
Houston, TX 77098

PRINCIPAL DISPLAY PANEL - 118 ml Bottle Carton

Day Time

Tukol®

HONEY MULTI SYMPTOM

COLD & FLU

Acetaminophen / Dextromethorphan HBr
/ Phenylephrine HCl

Ages
12+

NATURAL
HONEY
FLAVOR

Relieves:

- HEADACHE, SORE THROAT, FEVER
- MINOR ACHES AND PAINS
- NASAL CONGESTION AND COUGH

4 FL OZ (118 ml)